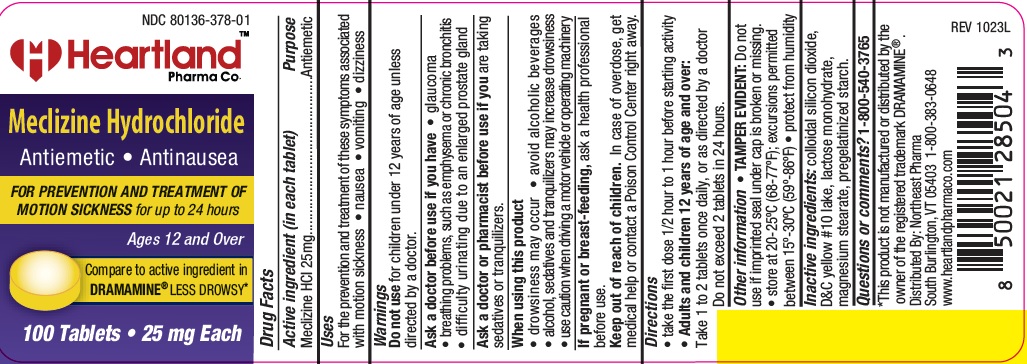 DRUG LABEL: Meclizine Hydrochloride
NDC: 80136-378 | Form: TABLET
Manufacturer: NORTHEAST PHARMA
Category: otc | Type: HUMAN OTC DRUG LABEL
Date: 20231114

ACTIVE INGREDIENTS: MECLIZINE HYDROCHLORIDE 25 mg/1 1
INACTIVE INGREDIENTS: LACTOSE MONOHYDRATE; SILICON DIOXIDE; STARCH, CORN; MAGNESIUM STEARATE; D&C YELLOW NO. 10 ALUMINUM LAKE

hpc 778L (378)

Active ingredient (in each tablet)

Meclizine HCI 25mg

Purpose

Antiemetic

Uses

For the prevention and treatment of these symptoms associated with motion sickness • nausea • vomiting • dizziness

Warnings

Do not use in children under 12 years of age unless directed by a doctor.

Ask a doctor before use if you have

• breathing problems, such as emphysema or chronic bronchitis

• glaucoma

• difficulty urinating due to an enlarged prostate gland

A sk a doctor or pharmacist before use if you are taking sedatives or tranquilizers.

When using this product
• drowsiness may occur

• avoid alcoholic beverages

• alcohol, sedatives and tranquilizers may increase drowsiness

• use caution when driving a motor vehicle or operating machinery
I f pregnant or breast-feeding,ask a health professional before use.

Keep out of reach of children. In case of overdose, get medical help or contact a Poison Control Center right away.

Directions

- take the first dose 1/2 hour to 1 hour before starting activity
- Adults and children 12 years of age and over:

Take 1 to 2 tablets once daily, or as directed by a doctor
Do not exceed 2 tablets in 24 hours.

Other information

• TAMPER EVIDENT:Do not use if imprinted seal under cap is broken or missing.

• store at 20-25ºC (68-77ºF); excursions permitted between 15º-30ºC (59º-86ºF)

• protect from humidity

Inactive ingredients

colloidal silicon dioxide, D&C yellow #10 lake, lactose monohydrate, magnesium stearate, pregelatinized starch.

Questions or comments?

1-800-540-3765